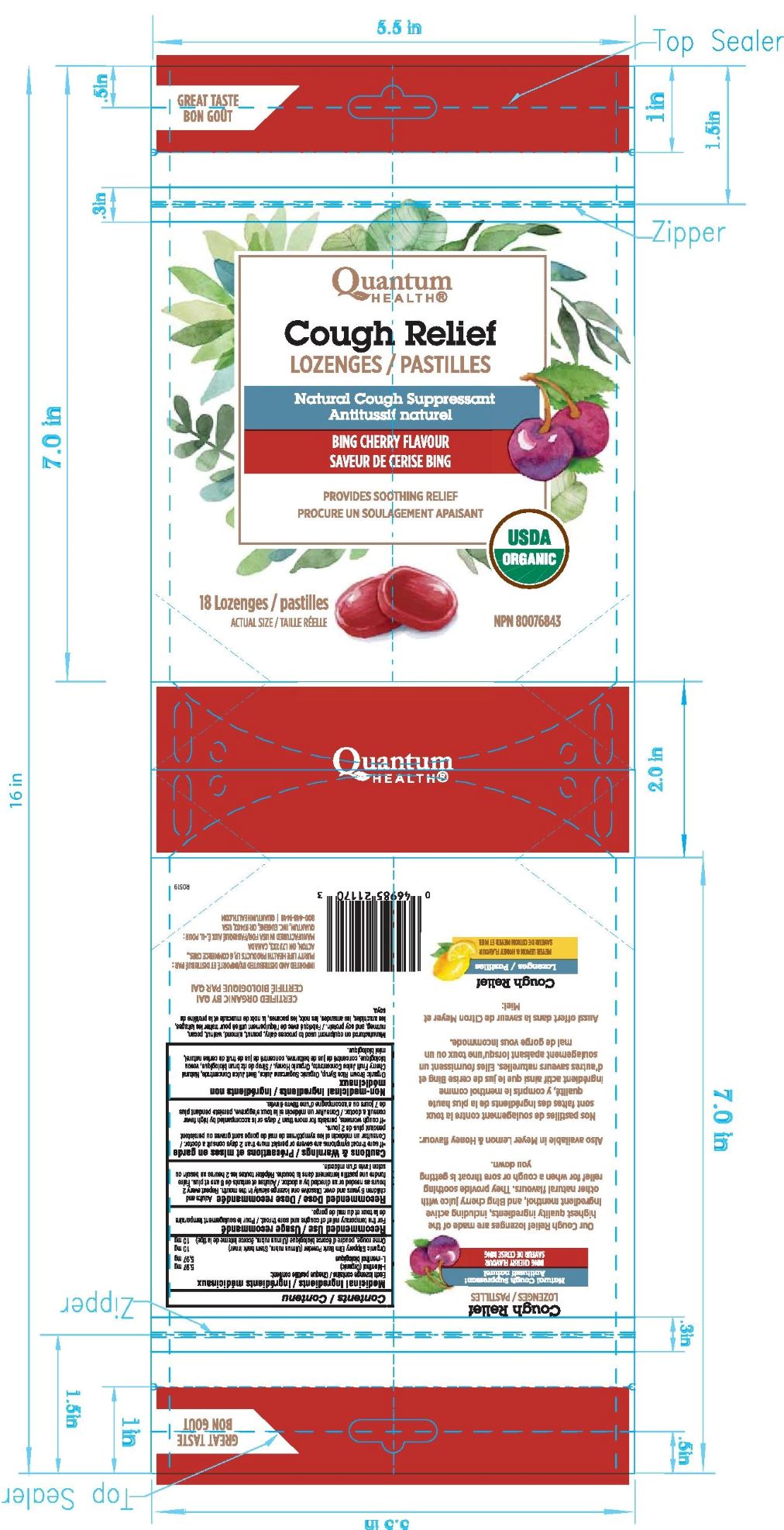 DRUG LABEL: Bing Cherry Cough Antitussif Relief
NDC: 70084-612 | Form: LOZENGE
Manufacturer: Quantum Inc.
Category: otc | Type: HUMAN OTC DRUG LABEL
Date: 20230110

ACTIVE INGREDIENTS: MENTHOL 5 mg/1 1
INACTIVE INGREDIENTS: BEET JUICE; CHERRY JUICE; HONEY; ULMUS RUBRA BARK; SUGARCANE; BARLEY MALT SYRUP

Bing Cherry-Cough Antitussif Relief Lozenges

ACTIVE INGREDIENT

Medicinal Ingredients:

Each lozenge contains:

I-Menthol 5.97mg

Organic Slippery Elm Bark Pwder (Ulmus rubra, Stem bark inner) 10mg

PURPOSE

Antitussif

DOSAGE AND ADMINISTRATION

Recommended Dose:

Adults and children 6 years and over. Dissolve one lozenge slowly in the mouth. Repeat every 2 hours as needed or as directed by a doctor.

Cautions & Warnings:

- If sore throat symptoms are severe or persist more than 2 days consult a doctor.

- If cough worsens, persists more than 7 days or is accompanied by high fever consult a doctor.

INACTIVE INGREDIENT

Non-Medicinal Ingredients:

Organic Brown Rice Syrup, Organic Sugarcane juice, Beet juice concentrate, Natural Cherry Fruit Juice Concentrate, Organic honey.

Keep out of reach of children

INDICATIONS AND USAGE

Recommended Use

For the temporary relief of coughs and sore throat.